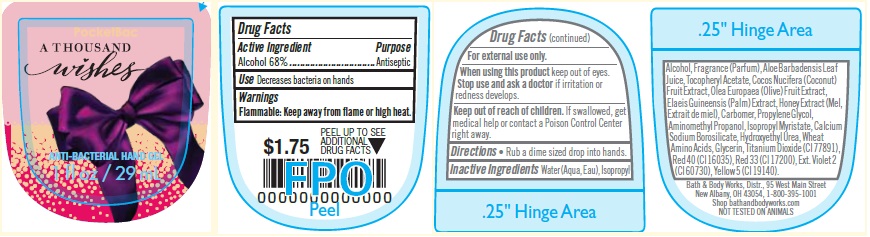 DRUG LABEL: Anti-Bacterial Hand
NDC: 62670-5138 | Form: GEL
Manufacturer: Bath & Body Works, Inc.
Category: otc | Type: HUMAN OTC DRUG LABEL
Date: 20161231

ACTIVE INGREDIENTS: ALCOHOL 68 mL/100 mL
INACTIVE INGREDIENTS: WATER

ACTIVE INGREDIENT

Alcohol 68%

PURPOSE

Antiseptic

USE

Decreases bacteria on hands.

WARNINGS

For external use only.

WHEN USING THIS PRODUCT

keep out of eyes.

STOP USE AND ASK A DOCTOR

if irritation or redness develops.

FLAMMABLE

Keep away from flame or high heat.

KEEP OUT OF REACH OF CHILDREN

If swallowed, get medical help or contact a Poison Control Center right away.

DIRECTIONS

- Rub a dime sized drop into hands.

INACTIVE INGREDIENTS

Water (Aqua, Eau), Isopropyl Alcohol, Fragrance (Parfum), Aloe Barbadensis Leaf Juice, Tocopheryl Acetate, Cocos Nucifera (Coconut)
Fruit Extract, Olea Europaea (Olive) Fruit Extract, Elaeis Guineensis (Palm) Extract, Honey Extract (Mel, Extrait de miel), Carbomer, Propylene Glycol, Aminomethyl Propanol, Isopropyl Myristate, Calcium Sodium Borosilicate, Hydroxyethyl Urea, Wheat Amino Acids, Glycerin, Titanium Dioxide (CI 77891), Red 40 (CI 16035), Red 33 (CI 17200), Ext. Violet 2 (CI 60730), Yellow 5 (CI 19140).

COMPANY INFORMATION

Bath & Body Works, Distr., 95 West Main Street

New Albany, OH, 43054, 1-800-395-1001

Shop 24/7 at www.bathandbodyworks.com